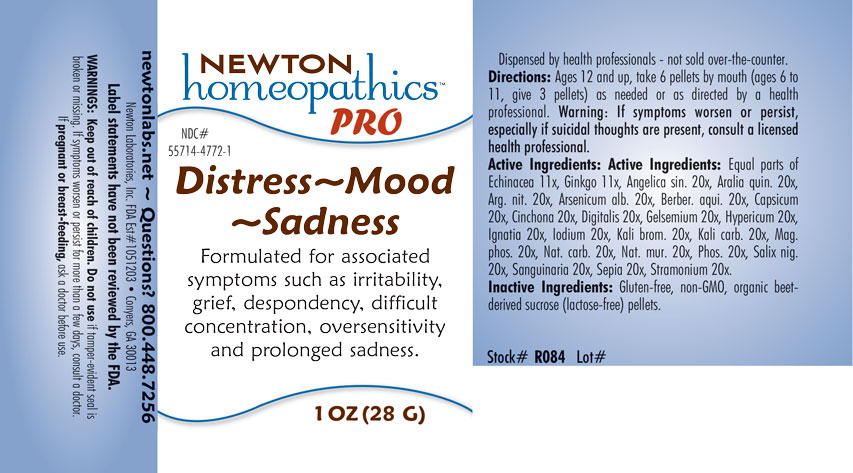 DRUG LABEL: Distress-Mood-Sadness
NDC: 55714-4772 | Form: PELLET
Manufacturer: Newton Laboratories, Inc.
Category: homeopathic | Type: HUMAN OTC DRUG LABEL
Date: 20201202

ACTIVE INGREDIENTS: ANGELICA SINENSIS ROOT 20 [hp_X]/1 g; AMERICAN GINSENG 20 [hp_X]/1 g; SILVER NITRATE 20 [hp_X]/1 g; ARSENIC TRIOXIDE 20 [hp_X]/1 g; CAPSICUM 20 [hp_X]/1 g; CINCHONA OFFICINALIS BARK 20 [hp_X]/1 g; DIGITALIS 20 [hp_X]/1 g; GELSEMIUM SEMPERVIRENS ROOT 20 [hp_X]/1 g; HYPERICUM PERFORATUM 20 [hp_X]/1 g; STRYCHNOS IGNATII SEED 20 [hp_X]/1 g; IODINE 20 [hp_X]/1 g; POTASSIUM BROMIDE 20 [hp_X]/1 g; POTASSIUM CARBONATE 20 [hp_X]/1 g; MAGNESIUM PHOSPHATE, DIBASIC TRIHYDRATE 20 [hp_X]/1 g; SODIUM CARBONATE 20 [hp_X]/1 g; SODIUM CHLORIDE 20 [hp_X]/1 g; PHOSPHORUS 20 [hp_X]/1 g; SALIX NIGRA BARK 20 [hp_X]/1 g; SANGUINARIA CANADENSIS ROOT 20 [hp_X]/1 g; SEPIA OFFICINALIS JUICE 20 [hp_X]/1 g; DATURA STRAMONIUM 20 [hp_X]/1 g; ECHINACEA, UNSPECIFIED 11 [hp_X]/1 g; GINKGO 11 [hp_X]/1 g; BERBERIS AQUIFOLIUM ROOT BARK 20 [hp_X]/1 g
INACTIVE INGREDIENTS: SUCROSE

Distress 4772P

INDICATIONS & USAGE SECTION

Distress - Mood - Sadness Formulated for associated symptoms such as irritability, grief, despondency, difficult concentration, oversensitivity and prolonged sadness.

DOSAGE & ADMINISTRATION SECTION

Directions: Ages 12 and up, take 6 pellets by mouth (ages 6 to 11, give 3 pellets) as needed or as directed by a health professional. Sensitive persons begin with 1 pellet and gradually increase to full dose. Warning: If symptoms worsen or persist, especially if suicidal thoughts are present, consult a licensed health professional.

OTC - ACTIVE INGREDIENT SECTION

Equal parts of Echinacea 11x, Ginkgo 11x, Angelica sin. 20x, Aralia quin. 20x, Arg. nit. 20x, Arsenicum alb. 20x, Berber. aqui. 20x, Capsicum 20x, Cinchona 20x, Digitalis 20x, Gelsemium 20x, Hypericum 20x, Ignatia 20x, Iodium 20x, Kali brom. 20x, Kali carb. 20x, Mag. phos. 20x, Nat. carb. 20x, Nat. mur. 20x, Phos. 20x, Salix nigra 20x, Sanguinaria 20x, Sepia 20x, Stramonium 20x.

OTC - PURPOSE SECTION

Formulated for associated symptoms such as irritability, grief, despondency, difficult concentration, oversensitivity and prolonged sadness.

INACTIVE INGREDIENT SECTION

Inactive Ingedients: Gluten-free, non-GMO, organc beet-derived sucrose (lactose-free) pellets.

QUESTIONS SECTION

newtonlabs.net - Questions? 800 448-7256

Newton Laboratories, Inc. FDA Est # 1051203 - Conyers, GA 30013

WARNINGS SECTION

WARNINGS: Keep out of reach of children. Do not use if taper-evident seal is broken or missing. If symptoms worsen or persist for more than few days, consult a doctor. If pregnant or breast-feeding, ask a doctor before use.

OTC - KEEP OUT OF REACH OF CHILDREN SECTION

Keep out of reach of children.

OTC - PREGNANCY OR BREAST FEEDING SECTION

If pregnant or breast-feeding, ask a doctor before use.